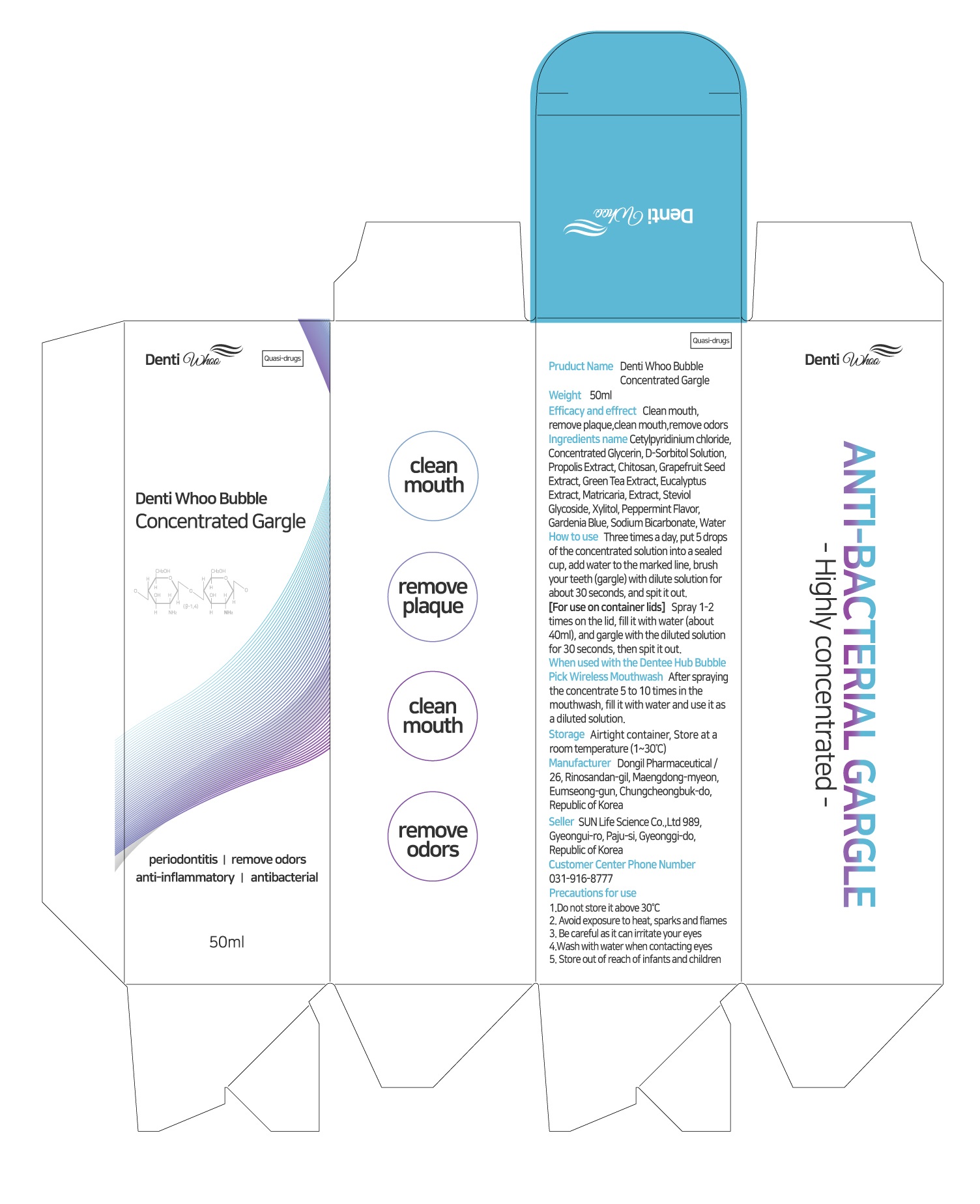 DRUG LABEL: Denti Whoo Bubble Concentrated Gargle
NDC: 86157-0004 | Form: LIQUID
Manufacturer: SUN LIFE SCIENCE CO LTD
Category: otc | Type: HUMAN OTC DRUG LABEL
Date: 20220406

ACTIVE INGREDIENTS: CETYLPYRIDINIUM CHLORIDE 2.296 g/100 mL
INACTIVE INGREDIENTS: XYLITOL; WATER; GLYCERIN

ACTIVE INGREDIENT

Cetylpyridinium chloride

INACTIVE INGREDIENT

Concentrated Glycerin
D-Sorbitol Solution
Propolis Extract
Chitosan
Grapefruit Seed Extract
Green Tea Extract
Eucalyptus Extract
Matricaria Extract
Steviol Glycoside
Xylitol
Peppermint Flavor
Gardenia Blue
Sodium Bicarbonate
Water

PURPOSE

Clean mouth, remove plaque, clean mouth, remove odors

Keep out of reach of children

INDICATIONS AND USAGE

Three times a day, put 5 drops of the concentrated solution into a sealed cup, addwater to the marked line, brush your teeth (gargle) with dilute solution for about 30seconds, and spit it out

WARNINGS

1.Do not store it above 30°C2. Avoid exposure to heat, sparks and flames3. Be careful as it can irritate your eyes4.Wash with water when contacting eyes5. Store out of reach of infants and children

DOSAGE AND ADMINISTRATION

For dental use only